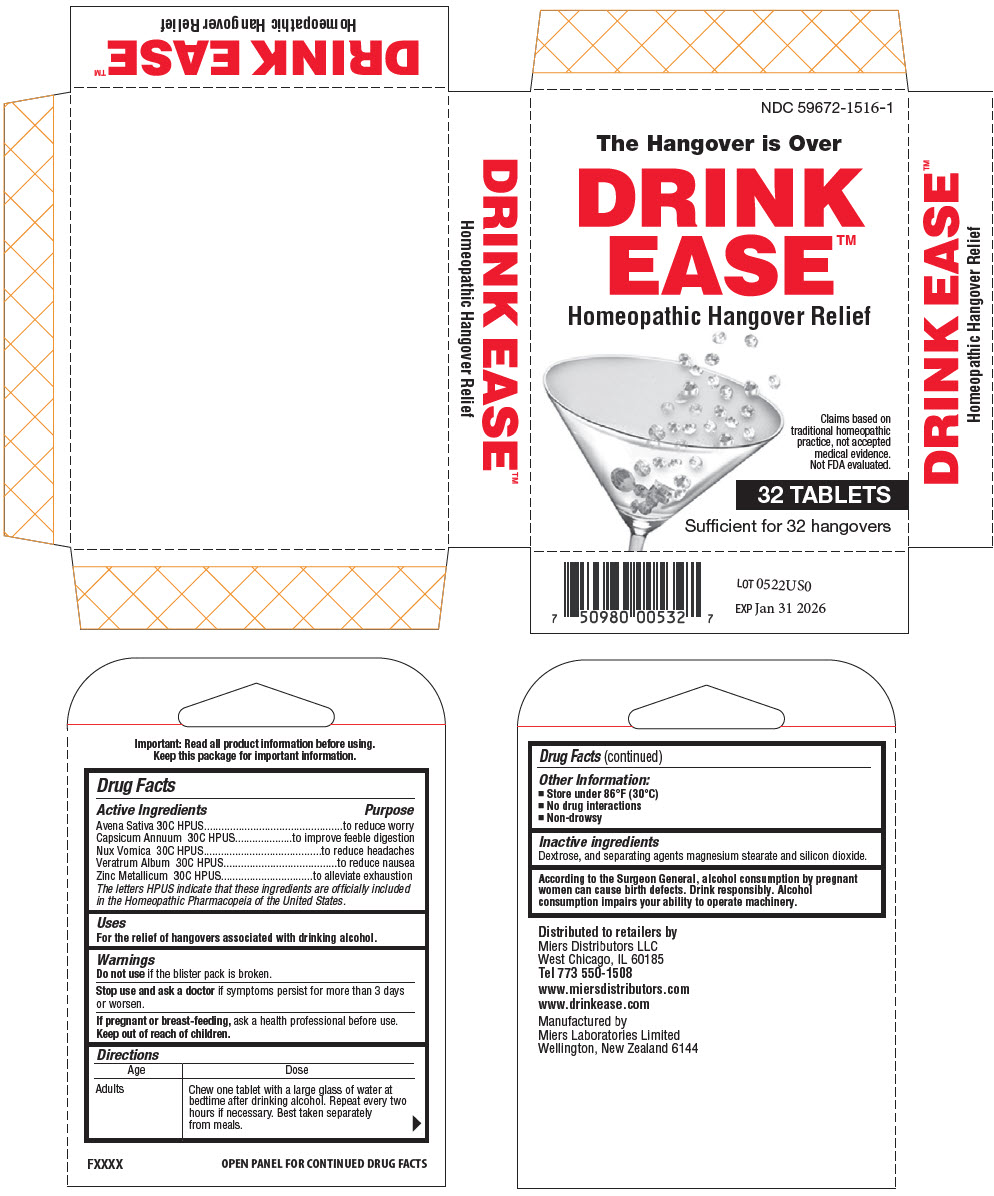 DRUG LABEL: Drink Ease
NDC: 59672-1516 | Form: TABLET
Manufacturer: Miers Laboratories
Category: homeopathic | Type: HUMAN OTC DRUG LABEL
Date: 20220204

ACTIVE INGREDIENTS: AVENA SATIVA FLOWERING TOP 30 [hp_C]/1 1; CAPSICUM 30 [hp_C]/1 1; STRYCHNOS NUX-VOMICA SEED 30 [hp_C]/1 1; VERATRUM ALBUM ROOT 30 [hp_C]/1 1; ZINC 30 [hp_C]/1 1
INACTIVE INGREDIENTS: DEXTROSE, UNSPECIFIED FORM 250 mg/1 1; SILICON DIOXIDE; MAGNESIUM STEARATE

Drink Ease™ 16 tablet bulk

Drug Facts

ACTIVE INGREDIENT

Active Ingredients | Purpose
Avena Sativa 30C HPUS | to reduce worry
Capsicum Annuum 30C HPUS | to improve feeble digestion
Nux Vomica 30C HPUS | to reduce headaches
Veratrum Album 30C HPUS | to reduce nausea
Zinc Metallicum 30C HPUS | to alleviate exhaustion
The letters HPUS indicate that these ingredients are officially included in the Homeopathic Pharmacopeia of the United States.

Uses

For the relief of hangovers associated with drinking alcohol.

Warnings

Do not use if the blister pack is broken.

Stop use and ask a doctor if symptoms persist for more than 3 days or worsen.

PREGNANCY OR BREAST FEEDING

If pregnant or breast-feeding, ask a health professional before use.

Keep out of reach of children.

Directions

Age | Dose
Adults | Chew one tablet with a large glass of water at bedtime after drinking alcohol. Repeat every two hours if necessary. Best taken separately from meals.

Other Information

- Store under 86°F (30°C)
- No drug interactions
- Non-drowsy

Inactive ingredients

Dextrose, and separating agents magnesium stearate and silicon dioxide.

According to the Surgeon General, alcohol consumption by pregnant women can cause birth defects. Drink responsibly. Alcohol consumption impairs your ability to operate machinery.

Distributed to retailers by
Miers Distributors LLC
West Chicago, IL 60185

Manufactured by
Miers Laboratories Limited
Wellington, New Zealand 6144

PRINCIPAL DISPLAY PANEL - 32 Tablet Blister Pack Box

NDC 59672-1516-1

The Hangover is Over

DRINK
EASE™
Homeopathic Hangover Relief

Claims based on
traditional homeopathic
practice, not accepted
medical evidence.
Not FDA evaluated.

32 TABLETS

Sufficient for 32 hangovers